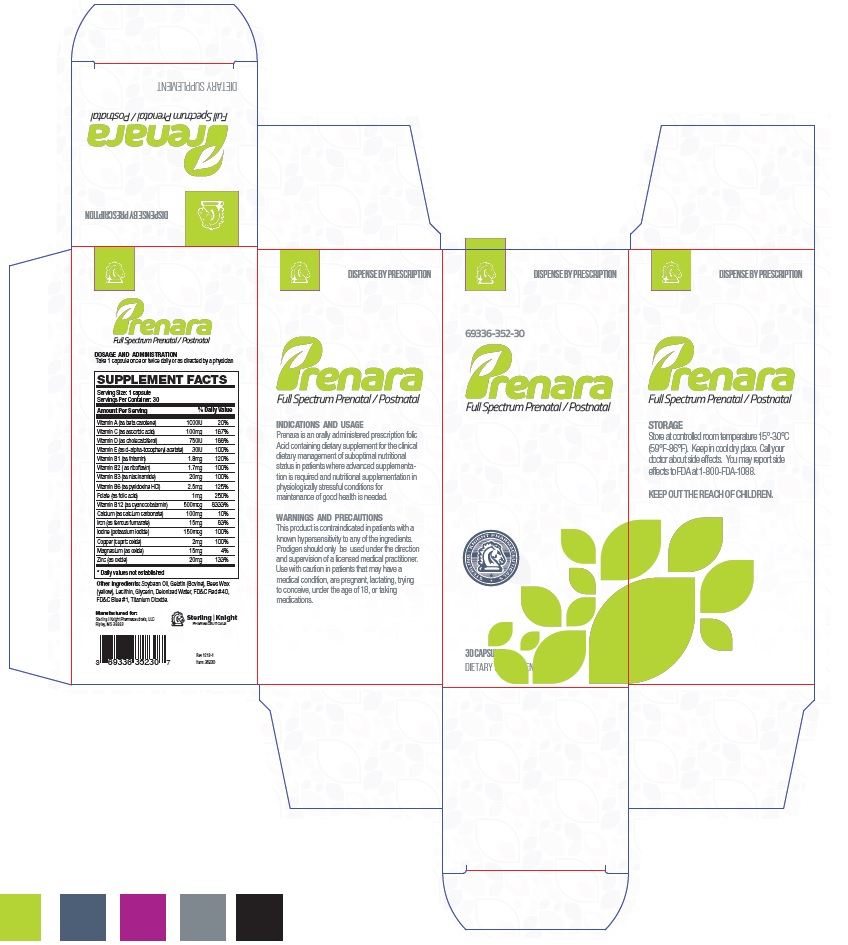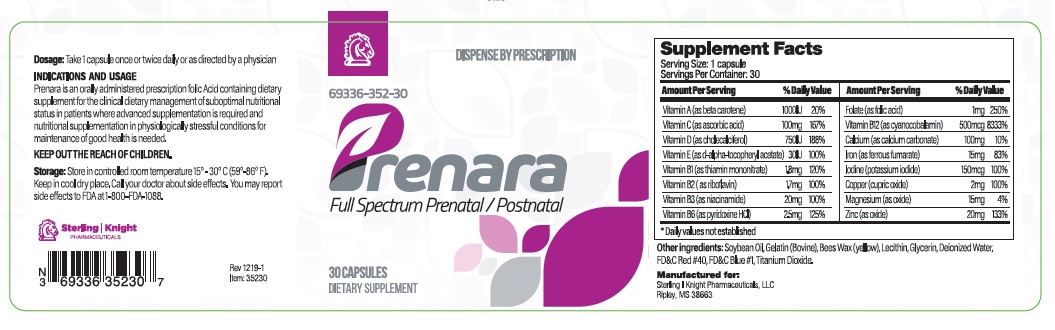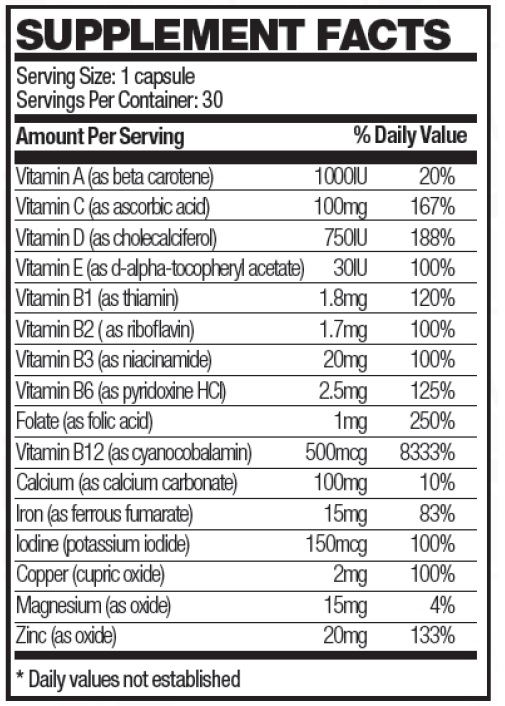 DRUG LABEL: Prenara
NDC: 69336-352 | Form: CAPSULE
Manufacturer: Sterling-Knight Pharmaceuticals, LLC
Category: prescription | Type: HUMAN PRESCRIPTION DRUG LABEL
Date: 20200303

ACTIVE INGREDIENTS: VITAMIN A 1000 [iU]/1 1; ASCORBIC ACID 100 mg/1 1; VITAMIN D 750 [iU]/1 1; THIAMINE 1.8 mg/1 1; RIBOFLAVIN 1.7 mg/1 1; NIACINAMIDE 20 mg/1 1; PYRIDOXINE HYDROCHLORIDE 2.5 mg/1 1; FOLIC ACID 1 mg/1 1; CYANOCOBALAMIN 0.5 mg/1 1; CALCIUM 100 mg/1 1; IODINE 0.15 mg/1 1; COPPER 2 mg/1 1; MAGNESIUM 15 mg/1 1; ZINC 20 mg/1 1

Prenara Capsules
Dietary Supplement

DESCRIPTION:

Prenara is an orally administered prescription dietary supplement formulation for the clinical dietary management of suboptimal nutritional status in patients where advanced supplementation is required and nutritional supplementation in physiologically stressful conditions for maintenance of good health is needed.
Prenara is a prescription dietary supplement for use throughout pregnancy, during the prenatal and postnatal period for both lactating and non-lactating mothers and throughout the childbearing years.
Prenara should be administered under the supervision of a licensed medical practitioner.

Each softgel capsule contains:

Other Ingredients: Soybean oil, gelatin (bovine), bees wax (yellow), lecithin, glycerin, deionized water, FD&C red #40, FD&C blue #1, titanium dioxide.

INDICATIONS AND USAGE:

Prenara is a prescription dietary supplement for use throughout pregnancy, during the prenatal and postnatal period for both lactating and non-lactating mothers and throughout the childbearing years

CONTRAINDICATIONS:

This product is contraindicated in patients with a known hypersensitivity to any of the ingredients.

Prenara should only be used under the direction and supervision of a licensed medical practitioner. Use with caution in patients that may have a medical condition, are pregnant, lactating, trying to conceive, under the age of 18, or taking medications.

WARNINGS AND PRECAUTIONS:

This product should be administered with caution in patients with a history of liver disease, jaundice or diabetes mellitus.

Folic acid above 1mg daily may obscure pernicious anemia in that hematologic remission may occur while neurological manifestations remain progressive.

WARNING: Accidental overdose of iron-containing products is a leading cause of fatal poisoning in children under 6. KEEP THIS AND ALL DRUGS OUT OF THE REACH OF CHILDREN. In case of accidental overdose, call a doctor or poison control center immediately.

KEEP THIS AND ALL MEDICATIONS OUT OF THE REACH OF CHILDREN.

ADVERSE REACTION:

Allergic sensitization has been reported following both oral and parental administration of folic acid.

DOSAGE AND ADMINISTRATION:

Usual dose is 1 to 2 capsules daily or as prescribed by licensed medical practitioner.

HOW SUPPLIED:

Prenara is supplied as a purple softgel capsules with 352 printed and dispensed in white HDPE plastic bottles of 30ct.

69336-352-30

STORAGE:

Store at controlled room temperature 15°-30°C (59°F-86°F). Keep in cool dry place. Call your doctor about side effects. You may report side effects to FDA at 1-800-FDA-1088. KEEP THIS OUT OF THE REACH OF CHILDREN.

Reserved for Professional Recommendation

All prescriptions using this product shall be pursuant to state statutes as applicable. This is not an Orange Book product. This product may be administered only under a physician’s supervision. There are no implied or explicit claims on therapeutic equivalence.

Manufactured for:
Sterling-Knight Pharmaceuticals, LLC
Ripley, MS 38663

Item 35230 Rev. 0320-1

Prenara Label

PACKAGE LABEL

Prenara Carton